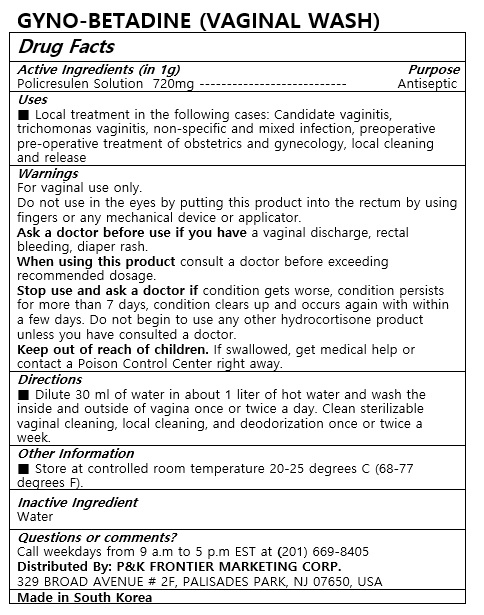 DRUG LABEL: GYNO-BETADINE
NDC: 72689-0041 | Form: SOLUTION
Manufacturer: OASIS TRADING
Category: otc | Type: HUMAN OTC DRUG LABEL
Date: 20190320

ACTIVE INGREDIENTS: POVIDONE-IODINE 10 g/100 mL
INACTIVE INGREDIENTS: WATER

ACTIVE INGREDIENT

POVIDONE-IODINE

PURPOSE

Local treatment in the following cases: Candidate vaginitis, trichomonas vaginitis, non-specific and mixed infection, preoperative pre-operative treatment of obstetrics and gynecology, local cleaning and release

Keep out of reach of children

INDICATIONS AND USAGE

Dilute 30 ml of water in about 1 liter of hot water and wash the inside and outside of vagina once or twice a day.Clean sterilizable vaginal cleaning, local cleaning, and deodorization once or twice a week.

Do not use
in the eyes
as a first aid antiseptic longer than one week
on individuals who are allergic or sensitive to iodine
over large areas of the body
Keep out of reach of children.
If swallowed, get medical help or contact a Poison Control Center right away.

INACTIVE INGREDIENT

Water, etc.

DOSAGE AND ADMINISTRATION

For vaginal use only